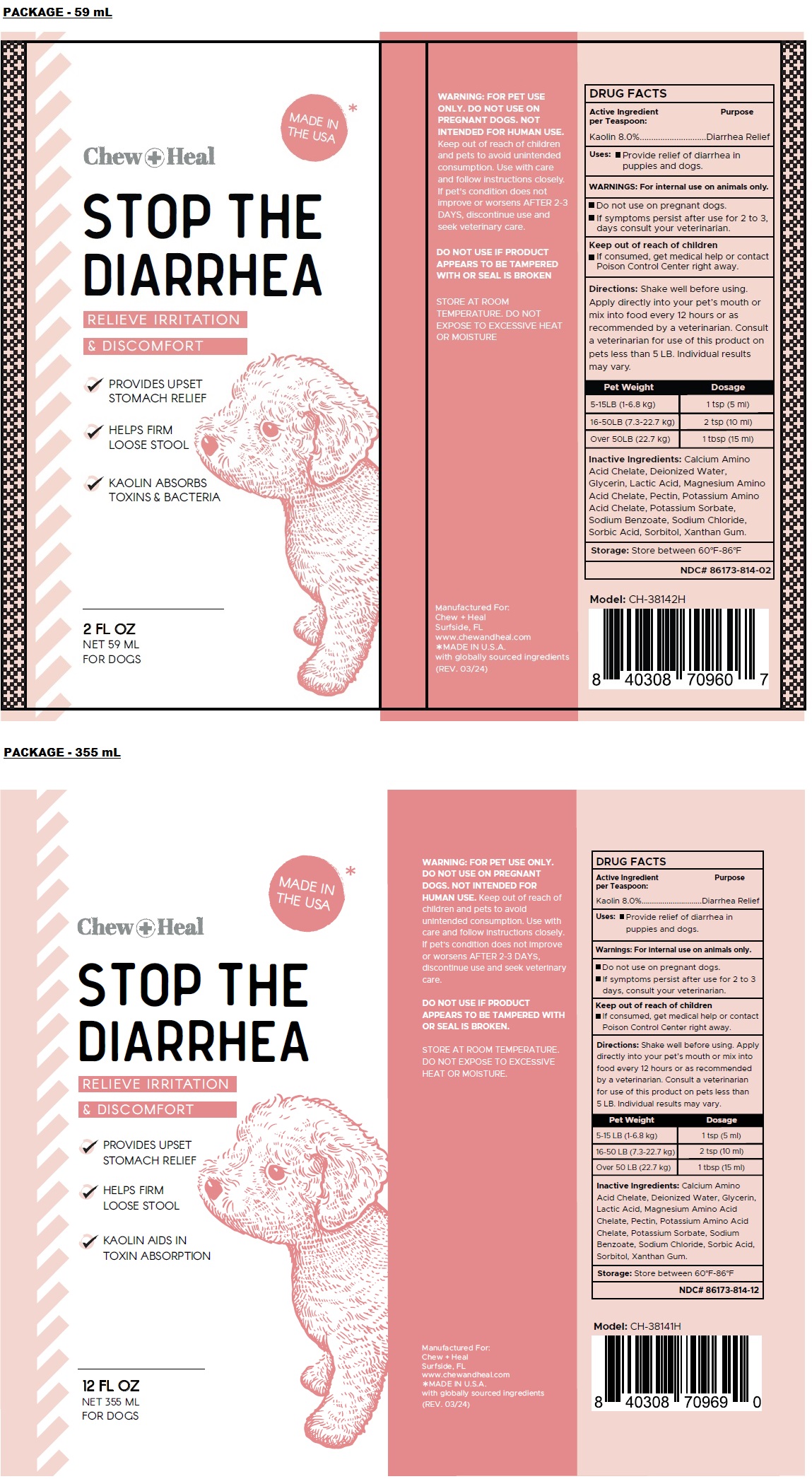 DRUG LABEL: STOP THE DIARRHEA
NDC: 86173-814 | Form: LIQUID
Manufacturer: Click Industries LLC
Category: animal | Type: OTC ANIMAL DRUG LABEL
Date: 20240315

ACTIVE INGREDIENTS: KAOLIN 8 g/100 mL
INACTIVE INGREDIENTS: CALCIUM; WATER; GLYCERIN; LACTIC ACID, UNSPECIFIED FORM; MAGNESIUM; PECTIN; POTASSIUM; POTASSIUM SORBATE; SODIUM BENZOATE; SODIUM CHLORIDE; SORBIC ACID; SORBITOL; XANTHAN GUM

Chew + Heal STOP THE DIARRHEA

Active Ingredient per Teaspoon:

Kaolin 8.0%

Purpose

Diarrhea Relief

Uses:

• Provide relief of diarrhea in puppies and dogs.

WARNINGS:

For internal use on animals only.

• Do not use on pregnant dogs.
• If symptoms persist after use for 2 to 3, days consult your veterinarian.

Keep out of reach of children
• If consumed, get medical help or contact Poison Control Center right away.

Directions:

Shake well before using. Apply directly into your pet's mouth or mix into food every 12 hours or as recommended by a veterinarian. Consult a veterinarian for use of this product on pets less than 5 LB. Individual results may vary.

Pet Weight | Dosage
5-15LB (1-6.8 kg) | 1 tsp (5 ml)
16-50LB (7.3-22.7 kg) | 2 tsp (10 ml)
Over 50LB (22.7 kg) | 1 tbsp (15 ml)

Inactive Ingredients:

Calcium Amino Acid Chelate, Deionized Water, Glycerin, Lactic Acid, Magnesium Amino Acid Chelate, Pectin, Potassium Amino Acid Chelate, Potassium Sorbate, Sodium Benzoate, Sodium Chloride, Sorbic Acid, Sorbitol, Xanthan Gum.

Storage:

Store between 60°F-86°F

MADE IN THE USA*

RELIEVE IRRITATION & DISCOMFORT

PROVIDES UPSET STOMACH RELIEF

HELPS FIRM LOOSE STOOL

KAOLIN ABSORBS TOXINS & BACTERIA

FOR DOGS

NOT INTENDED FOR HUMAN USE.

Keep out of reach of children and pets to avoid unintended consumption. Use with care and follow instructions closely.

DO NOT USE IF PRODUCT APPEARS TO BE TAMPERED WITH OR SEAL IS BROKEN

STORE AT ROOM TEMPERATURE. DO NOT EXPOSE TO EXCESSIVE HEAT OR MOISTURE

Manufactured For:
Chew + Heal
Surfside, FL
www.chewandheal.com
*MADE IN U.S.A. with globally sourced ingredients